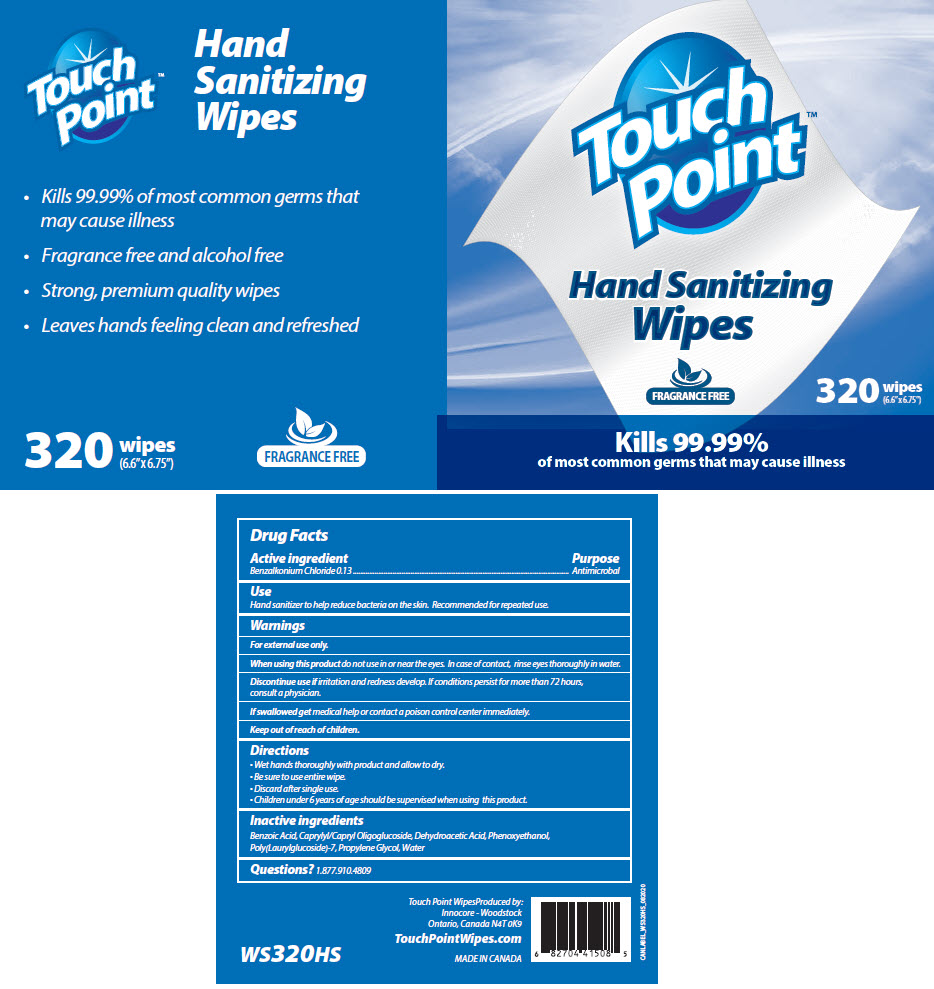 DRUG LABEL: Touchpoint Hand Sanitizing Wipes Fragrance Free
NDC: 70924-003 | Form: CLOTH
Manufacturer: Innocore Sales & Marketing Inc
Category: otc | Type: HUMAN OTC DRUG LABEL
Date: 20250619

ACTIVE INGREDIENTS: BENZALKONIUM CHLORIDE 1.3 mg/1 1
INACTIVE INGREDIENTS: CAPRYLYL/CAPRYL OLIGOGLUCOSIDE; DEHYDROACETIC ACID; PHENOXYETHANOL; BENZOIC ACID; POLY(LAURYLGLUCOSIDE)-7; PROPYLENE GLYCOL; WATER

Touchpoint™ Hand Sanitizing Wipes Fragrance Free

Drug Facts

Active ingredient

Benzalkonium Chloride 0.13

Purpose

Antimicrobal

Use

Hand sanitizer to help reduce bacteria on the skin. Recommended for repeated use.

Warnings

For external use only.

WHEN USING

When using this productdo not use in or near the eyes. In case of contact, rinse eyes thoroughly in water.

DO NOT USE

Discontinue use ifirritation and redness develop. If conditions persist for more than 72 hours, consult a physician.

If swallowed getmedical help or contact a poison control center immediately.

Keep out of reach of children.

Directions

- Wet hands thoroughly with product and allow to dry.
- Be sure to use entire wipe.
- Discard after single use.
- Children under 6 years of age should be supervised when using this product.

Inactive ingredients

Benzoic Acid, Caprylyl/Capryl Oligoglucoside, Dehydroacetic Acid, Phenoxyethanol, Poly(Laurylglucoside)-7, Propylene Glycol, Water

Questions?

1.877.910.4809

PACKAGE LABEL

Touch
Point™

Hand Sanitizing
Wipes

FRAGRANCE FREE

320
wipes
(6.6" x 6.75")

Kills 99.99%
of most common germs that may cause illness